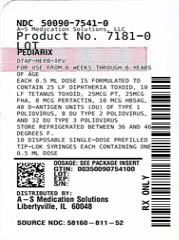 DRUG LABEL: PEDIARIX
NDC: 50090-7541 | Form: INJECTION, SUSPENSION
Manufacturer: A-S Medication Solutions
Category: other | Type: VACCINE LABEL
Date: 20250813

ACTIVE INGREDIENTS: CORYNEBACTERIUM DIPHTHERIAE TOXOID ANTIGEN (FORMALDEHYDE INACTIVATED) 25 [iU]/0.5 mL; CLOSTRIDIUM TETANI TOXOID ANTIGEN (FORMALDEHYDE INACTIVATED) 10 [iU]/0.5 mL; BORDETELLA PERTUSSIS TOXOID ANTIGEN (FORMALDEHYDE, GLUTARALDEHYDE INACTIVATED) 25 ug/0.5 mL; BORDETELLA PERTUSSIS FILAMENTOUS HEMAGGLUTININ ANTIGEN (FORMALDEHYDE INACTIVATED) 25 ug/0.5 mL; BORDETELLA PERTUSSIS PERTACTIN ANTIGEN (FORMALDEHYDE INACTIVATED) 8 ug/0.5 mL; HEPATITIS B VIRUS SUBTYPE ADW2 HBSAG SURFACE PROTEIN ANTIGEN 10 ug/0.5 mL; POLIOVIRUS TYPE 1 ANTIGEN (FORMALDEHYDE INACTIVATED) 40 [iU]/0.5 mL; POLIOVIRUS TYPE 2 ANTIGEN (FORMALDEHYDE INACTIVATED) 8 [iU]/0.5 mL; POLIOVIRUS TYPE 3 ANTIGEN (FORMALDEHYDE INACTIVATED) 32 [iU]/0.5 mL
INACTIVE INGREDIENTS: FORMALDEHYDE; SODIUM CHLORIDE; ALUMINUM HYDROXIDE; ALUMINUM PHOSPHATE; PEG-20 SORBITAN OLEATE

HIGHLIGHTS OF PRESCRIBING INFORMATION

These highlights do not include all the information needed to use PEDIARIX safely and effectively. See full prescribing information for PEDIARIX.
PEDIARIX [Diphtheria and Tetanus Toxoids and Acellular Pertussis Adsorbed, Hepatitis B (Recombinant) and Inactivated Poliovirus Vaccine], Suspension for Intramuscular Injection
Initial U.S. Approval: 2002

1 INDICATIONS AND USAGE

PEDIARIX is a vaccine indicated for active immunization against diphtheria, tetanus, pertussis, infection caused by all known subtypes of hepatitis B virus, and poliomyelitis. PEDIARIX is approved for use as a 3-dose series in infants born of hepatitis B surface antigen (HBsAg)-negative mothers. PEDIARIX may be given as early as 6 weeks of age through 6 years of age (prior to the seventh birthday). (1)

2 DOSAGE AND ADMINISTRATION

Three doses (0.5-mL each) by intramuscular injection at 2, 4, and 6 months of age. (2.2)

3 DOSAGE FORMS AND STRENGTHS

Single-dose, prefilled syringes containing a 0.5-mL suspension for injection. (3)

4 CONTRAINDICATIONS

- Severe allergic reaction (e.g., anaphylaxis) after a previous dose of any diphtheria toxoid-, tetanus toxoid-, pertussis-, hepatitis B-, or poliovirus-containing vaccine, or to any component of PEDIARIX. (4.1)
- Encephalopathy within 7 days of administration of a previous pertussis-containing vaccine. (4.2)
- Progressive neurologic disorders. (4.3)

5 WARNINGS AND PRECAUTIONS

- In clinical trials, PEDIARIX was associated with higher rates of fever, relative to separately administered vaccines. (5.1)
- If Guillain-Barré syndrome occurs within 6 weeks of receipt of a prior vaccine containing tetanus toxoid, the decision to give PEDIARIX should be based on potential benefits and risks. (5.2)
- Syncope (fainting) can occur in association with administration of injectable vaccines, including PEDIARIX. Procedures should be in place to avoid falling injury and to restore cerebral perfusion following syncope. (5.3)
- If temperature ≥105°F, collapse or shock-like state, or persistent, inconsolable crying lasting ≥3 hours have occurred within 48 hours after receipt of a pertussis-containing vaccine, or if seizures have occurred within 3 days after receipt of a pertussis-containing vaccine, the decision to give PEDIARIX should be based on potential benefits and risks. (5.4)
- For children at higher risk for seizures, an antipyretic may be administered at the time of vaccination with PEDIARIX. (5.5)
- Apnea following intramuscular vaccination has been observed in some infants born prematurely. Decisions about when to administer an intramuscular vaccine, including PEDIARIX, to infants born prematurely should be based on consideration of the individual infant’s medical status and the potential benefits and possible risks of vaccination. (5.6)

6 ADVERSE REACTIONS

Common solicited adverse reactions following any dose (≥25%) included local injection site reactions (pain, redness, and swelling), fever (≥100.4°F), drowsiness, irritability/fussiness, and loss of appetite. (6.1)

To report SUSPECTED ADVERSE REACTIONS, contact GlaxoSmithKline at 1-888-825-5249 or VAERS at 1-800-822-7967 or www.vaers.hhs.gov.

7 DRUG INTERACTIONS

Do not mix PEDIARIX with any other vaccine in the same syringe. (7.1)

FULL PRESCRIBING INFORMATION

1 INDICATIONS AND USAGE

PEDIARIX is indicated for active immunization against diphtheria, tetanus, pertussis, infection caused by all known subtypes of hepatitis B virus, and poliomyelitis. PEDIARIX is approved for use as a 3-dose series in infants born of hepatitis B surface antigen (HBsAg)-negative mothers. PEDIARIX may be given as early as 6 weeks of age through 6 years of age (prior to the seventh birthday).

2 DOSAGE AND ADMINISTRATION

2.1 Preparation for Administration

Shake vigorously to obtain a homogeneous, turbid, white suspension. Do not use if resuspension does not occur with vigorous shaking. Parenteral drug products should be inspected visually for particulate matter and discoloration prior to administration, whenever solution and container permit. If either of these conditions exists, the vaccine should not be administered.

Attach a sterile needle and administer intramuscularly.

The preferred administration site is the anterolateral aspect of the thigh for children younger than 1 year. In older children, the deltoid muscle is usually large enough for an intramuscular injection. The vaccine should not be injected in the gluteal area or areas where there may be a major nerve trunk. Gluteal injections may result in suboptimal hepatitis B immune response.

Do not administer this product intravenously, intradermally, or subcutaneously.

2.2 Recommended Dose and Schedule

Immunization with PEDIARIX consists of 3 doses of 0.5 mL each by intramuscular injection at 2, 4, and 6 months of age (at intervals of 6 to 8 weeks, preferably 8 weeks). The first dose may be given as early as 6 weeks of age. Three doses of PEDIARIX constitute a primary immunization course for diphtheria, tetanus, pertussis, and poliomyelitis and the complete vaccination course for hepatitis B.

2.3 Modified Schedules in Previously Vaccinated Children

Children Previously Vaccinated with Diphtheria and Tetanus Toxoids and Acellular Pertussis Vaccine Adsorbed (DTaP)

PEDIARIX may be used to complete the first 3 doses of the DTaP series in children who have received 1 or 2 doses of INFANRIX (Diphtheria and Tetanus Toxoids and Acellular Pertussis Vaccine Adsorbed), manufactured by GlaxoSmithKline, identical to the DTaP component of PEDIARIX [see Description (11)] and are also scheduled to receive the other vaccine components of PEDIARIX. Data are not available on the safety and effectiveness of using PEDIARIX following 1 or more doses of a DTaP vaccine from a different manufacturer.

Children Previously Vaccinated with Hepatitis B Vaccine

PEDIARIX may be used to complete the hepatitis B vaccination series following 1 or 2 doses of another hepatitis B vaccine (monovalent or as part of a combination vaccine), including vaccines from other manufacturers, in children born of HBsAg-negative mothers who are also scheduled to receive the other vaccine components of PEDIARIX.

A 3-dose series of PEDIARIX may be administered to infants born of HBsAg-negative mothers and who received a dose of hepatitis B vaccine at or shortly after birth. However, data are limited regarding the safety of PEDIARIX in such infants [see Adverse Reactions (6.1)]. There are no data to support the use of a 3-dose series of PEDIARIX in infants who have previously received more than 1 dose of hepatitis B vaccine.

Children Previously Vaccinated with Inactivated Poliovirus Vaccine (IPV)

PEDIARIX may be used to complete the first 3 doses of the IPV series in children who have received 1 or 2 doses of IPV from a different manufacturer and are also scheduled to receive the other vaccine components of PEDIARIX.

2.4 Booster Immunization following PEDIARIX

Children who have received a 3-dose series with PEDIARIX should complete the DTaP and IPV series according to the recommended schedule.^1 Because the pertussis antigens contained in INFANRIX and KINRIX (Diphtheria and Tetanus Toxoids and Acellular Pertussis Adsorbed and Inactivated Poliovirus Vaccine), manufactured by GlaxoSmithKline, are the same as those in PEDIARIX, these children should receive INFANRIX as their fourth dose of DTaP and either INFANRIX or KINRIX as their fifth dose of DTaP, according to the respective prescribing information for these vaccines. KINRIX or another manufacturer’s IPV may be used to complete the 4-dose IPV series according to the respective prescribing information.

3 DOSAGE FORMS AND STRENGTHS

PEDIARIX is a suspension for injection available in 0.5-mL single-dose prefilled TIP‑LOK syringes.

4 CONTRAINDICATIONS

4.1 Hypersensitivity

A severe allergic reaction (e.g., anaphylaxis) after a previous dose of any diphtheria toxoid-, tetanus toxoid-, pertussis antigen-, hepatitis B-, or poliovirus-containing vaccine or any component of this vaccine, including yeast, neomycin, and polymyxin B, is a contraindication to administration of PEDIARIX [see Description (11)].

4.2 Encephalopathy

Encephalopathy (e.g., coma, decreased level of consciousness, prolonged seizures) within 7 days of administration of a previous dose of a pertussis-containing vaccine that is not attributable to another identifiable cause is a contraindication to administration of any pertussis-containing vaccine, including PEDIARIX.

4.3 Progressive Neurologic Disorder

Progressive neurologic disorder, including infantile spasms, uncontrolled epilepsy, or progressive encephalopathy, is a contraindication to administration of any pertussis-containing vaccine, including PEDIARIX. PEDIARIX should not be administered to individuals with such conditions until the neurologic status is clarified and stabilized.

5 WARNINGS AND PRECAUTIONS

5.1 Fever

In clinical trials, administration of PEDIARIX in infants was associated with higher rates of fever relative to separately administered vaccines [see Adverse Reactions (6.1)].

5.2 Guillain-Barré Syndrome

If Guillain-Barré syndrome occurs within 6 weeks of receipt of a prior vaccine containing tetanus toxoid, the decision to give PEDIARIX or any vaccine containing tetanus toxoid should be based on careful consideration of the potential benefits and possible risks.

5.3 Syncope

Syncope (fainting) can occur in association with administration of injectable vaccines, including PEDIARIX. Syncope can be accompanied by transient neurological signs such as visual disturbance, paresthesia, and tonic-clonic limb movements. Procedures should be in place to avoid falling injury and to restore cerebral perfusion following syncope.

5.4 Adverse Reactions following Prior Pertussis Vaccination

If any of the following reactions occur in temporal relation to receipt of a vaccine containing a pertussis component, the decision to give any pertussis-containing vaccine, including PEDIARIX, should be based on careful consideration of the potential benefits and possible risks:

- Temperature of ≥40.5oC (105oF) within 48 hours not due to another identifiable cause;
- Collapse or shock-like state (hypotonic-hyporesponsive episode) within 48 hours;
- Persistent, inconsolable crying lasting ≥3 hours, occurring within 48 hours;
- Seizures with or without fever occurring within 3 days.

5.5 Children at Risk for Seizures

For children at higher risk for seizures than the general population, an appropriate antipyretic may be administered at the time of vaccination with a vaccine containing a pertussis component, including PEDIARIX, and for the ensuing 24 hours to reduce the possibility of post-vaccination fever.

5.6 Apnea in Premature Infants

Apnea following intramuscular vaccination has been observed in some infants born prematurely. Decisions about when to administer an intramuscular vaccine, including PEDIARIX, to infants born prematurely should be based on consideration of the individual infant’s medical status and the potential benefits and possible risks of vaccination.

5.7 Preventing and Managing Allergic Vaccine Reactions

Prior to administration, the healthcare provider should review the immunization history for possible vaccine sensitivity and previous vaccination-related adverse reactions to allow an assessment of benefits and risks. Epinephrine and other appropriate agents used for the control of immediate allergic reactions must be immediately available should an acute anaphylactic reaction occur.

6 ADVERSE REACTIONS

6.1 Clinical Trials Experience

Because clinical trials are conducted under widely varying conditions, adverse reaction rates observed in the clinical trials of a vaccine cannot be directly compared to rates in the clinical trials of another vaccine and may not reflect the rates observed in practice.

A total of 23,849 doses of PEDIARIX have been administered to 8,088 infants who received 1 or more doses as part of the 3-dose series during 14 clinical studies. Common adverse reactions that occurred in ≥25% of subjects following any dose of PEDIARIX included local injection site reactions (pain, redness, and swelling), fever, drowsiness, irritability/fussiness, and loss of appetite. In comparative studies (including the German and U.S. studies described below), administration of PEDIARIX was associated with higher rates of fever relative to separately administered vaccines [see Warnings and Precautions (5.1)]. The prevalence of fever was highest on the day of vaccination and the day following vaccination. More than 96% of episodes of fever resolved within the 4-day period following vaccination (i.e., the period including the day of vaccination and the next 3 days).

In the largest of the 14 studies conducted in Germany, safety data were available for 4,666 infants who received PEDIARIX administered concomitantly at separate sites with 1 of 4 Haemophilus influenzae type b (Hib) conjugate vaccines (GlaxoSmithKline [licensed in the United States only for booster immunization], Wyeth Pharmaceuticals Inc. [no longer licensed in the United States], Sanofi Pasteur SA [U.S.-licensed], or Merck & Co, Inc. [U.S.-licensed]) at 3, 4, and 5 months of age and for 768 infants in the control group that received separate U.S.-licensed vaccines (INFANRIX, Hib conjugate vaccine [Sanofi Pasteur SA], and oral poliovirus vaccine [OPV] [Wyeth Pharmaceuticals, Inc.; no longer licensed in the United States]). In this study, information on adverse events that occurred within 30 days following vaccination was collected. More than 95% of study participants were White.

In a U.S. study, the safety of PEDIARIX administered to 673 infants was compared with the safety of separately administered INFANRIX, ENGERIX-B [Hepatitis B Vaccine (Recombinant)], and IPV (Sanofi Pasteur SA) in 335 infants. In both groups, infants received Hib conjugate vaccine (Wyeth Pharmaceuticals Inc.; no longer licensed in the United States) and 7-valent pneumococcal conjugate vaccine (Wyeth Pharmaceuticals Inc.) concomitantly at separate sites. All vaccines were administered at 2, 4, and 6 months of age. Data on solicited local reactions and general adverse reactions were collected by parents using standardized diary cards for 4 consecutive days following each vaccine dose (i.e., day of vaccination and the next 3 days). Telephone follow-up was conducted 1 month and 6 months after the third vaccination to inquire about serious adverse events. At the 6-month follow-up, information also was collected on new onset of chronic illnesses. A total of 638 subjects who received PEDIARIX and 313 subjects who received INFANRIX, ENGERIX-B, and IPV completed the 6-month follow-up. Among subjects in both study groups combined, 69% were White, 18% were Hispanic, 7% were Black, 3% were Asian, and 3% were of other racial/ethnic groups.

Solicited Adverse Reactions

Data on solicited local reactions and general adverse reactions from the U.S. safety study are presented in Table 1. This study was powered to evaluate fever >101.3°F following Dose 1. The rate of fever ≥100.4°F following each dose was significantly higher in the group that received PEDIARIX compared with separately administered vaccines. Other statistically significant differences between groups in rates of fever, as well as other solicited adverse reactions, are noted in Table 1. Medical attention (a visit to or from medical personnel) for fever within 4 days following vaccination was sought in the group who received PEDIARIX for 8 infants after the first dose (1.2%), 1 infant following the second dose (0.2%), and 5 infants following the third dose (0.8%) (Table 1). Following Dose 2, medical attention for fever was sought for 2 infants (0.6%) who received separately administered vaccines (Table 1). Among infants who had a medical visit for fever within 4 days following vaccination, 9 of 14 who received PEDIARIX and 1 of 2 who received separately administered vaccines, had 1 or more diagnostic studies performed to evaluate the cause of fever.

Table 1. Percentage of Infants with Solicited Local and General Adverse Reactions within 4 Days of Vaccinationa at 2, 4, and 6 Months of Age with PEDIARIX Administered Concomitantly with Hib Conjugate Vaccine and 7-Valent Pneumococcal Conjugate Vaccine (PCV7) or with Separate Concomitant Administration of INFANRIX, ENGERIX-B, IPV, Hib Conjugate Vaccine, and PCV7 (Modified Intent-to-Treat Cohort)
Adverse Reaction | PEDIARIX, Hib Vaccine, & PCV7 |  |  | INFANRIX, ENGERIX-B, IPV, Hib Vaccine, & PCV7
Adverse Reaction | Dose 1 | Dose 2 | Dose 3 | Dose 1 | Dose 2 | Dose 3
Localb
n | 671 | 653 | 648 | 335 | 323 | 315
Pain, any | 36 | 36 | 31 | 32 | 30 | 30
Pain, Grade 2 or 3 | 12 | 11 | 11 | 9 | 9 | 9
Pain, Grade 3 | 2 | 3 | 2 | 3 | 2 | 1
Redness, any | 25c | 37 | 40 | 18 | 33 | 39
Redness, >5 mm | 6c | 10c | 13c | 2 | 6 | 7
Redness, >20 mm | 1 | 1c | 3 | 0 | 0 | 2
Swelling, any | 17c | 27c | 29 | 10 | 20 | 25
Swelling, >5 mm | 6c | 10c | 9c | 2 | 5 | 4
Swelling, >20 mm | 2 | 3c | 3 | 1 | 0 | 1
General
n | 667 | 644 | 645 | 333 | 321 | 311
Feverd, ≥100.4°F | 28c | 39c | 34c | 20 | 30 | 24
Feverd, >101.3°F | 7 | 14c | 9 | 5 | 10 | 6
Feverd, >102.2°F | 2c | 4 | 3 | 0 | 3 | 2
Feverd, >103.1°F | 1 | 1 | 1 | 0 | 0 | 0
Feverd, M.A. | 1c | 0 | 1 | 0 | 1 | 0
n | 671 | 653 | 648 | 335 | 323 | 315
Drowsiness, any | 57 | 52 | 41 | 54 | 48 | 38
Drowsiness, Grade 2 or 3 | 16 | 14 | 11 | 18 | 12 | 11
Drowsiness, Grade 3 | 3 | 1 | 1 | 4 | 1 | 2
Irritability/Fussiness, any | 61 | 65 | 61 | 62 | 62 | 57
Irritability/Fussiness, Grade 2 or 3 | 20 | 28c | 25c | 19 | 21 | 19
Irritability/Fussiness, Grade 3 | 3 | 4 | 4 | 4 | 3 | 3
Loss of appetite, any | 30 | 31 | 26 | 28 | 27 | 24
Loss of appetite, Grade 2 or 3 | 7 | 8c | 6 | 5 | 3 | 5
Loss of appetite, Grade 3 | 1 | 0 | 0 | 1 | 0 | 0
Hib conjugate vaccine (Wyeth Pharmaceuticals Inc.; no longer licensed in the United States); PCV7 (Wyeth Pharmaceuticals Inc.); IPV (Sanofi Pasteur SA).
Modified intent-to-treat cohort = All vaccinated subjects for whom safety data were available.
n = Number of infants for whom at least 1 symptom sheet was completed; for fever, numbers exclude missing temperature recordings or tympanic measurements.
M.A. = Medically attended (a visit to or from medical personnel).
Grade 2 defined as sufficiently discomforting to interfere with daily activities.
Grade 3 defined as preventing normal daily activities.
a Within 4 days of vaccination defined as day of vaccination and the next 3 days.
b Local reactions at the injection site for PEDIARIX or INFANRIX.
c Rate significantly higher in the group that received PEDIARIX compared with separately administered vaccines (P value <0.05 [2-sided Fisher Exact test] or the 95% CI on the difference between groups [Separate minus PEDIARIX] does not include 0).
d Axillary temperatures increased by 1°C and oral temperatures increased by 0.5°C to derive equivalent rectal temperature.

Serious Adverse Events

Within 30 days following any dose of vaccine in the U.S. safety study in which all subjects received concomitant Hib and pneumococcal conjugate vaccines, 7 serious adverse events were reported in 7 subjects (1% [7/673]) who received PEDIARIX (1 case each of pyrexia, gastroenteritis, and culture-negative clinical sepsis and 4 cases of bronchiolitis) and 5 serious adverse events were reported in 4 subjects (1% [4/335]) who received INFANRIX, ENGERIX-B, and IPV (uteropelvic junction obstruction and testicular atrophy in 1 subject and 3 cases of bronchiolitis).

Deaths

In 14 clinical trials, 5 deaths were reported among 8,088 (0.06%) recipients of PEDIARIX and 1 death was reported among 2,287 (0.04%) recipients of comparator vaccines. Causes of death in the group that received PEDIARIX included 2 cases of Sudden Infant Death Syndrome (SIDS) and 1 case of each of the following: convulsive disorder, congenital immunodeficiency with sepsis, and neuroblastoma. One case of SIDS was reported in the comparator group. The rate of SIDS among all recipients of PEDIARIX across the 14 trials was 0.25/1,000. The rate of SIDS observed for recipients of PEDIARIX in the German safety study was 0.2/1,000 infants (reported rate of SIDS in Germany in the latter part of the 1990s was 0.7/1,000 newborns). The reported rate of SIDS in the United States from 1990 to 1994 was 1.2/1,000 live births. By chance alone, some cases of SIDS can be expected to follow receipt of pertussis-containing vaccines.

Onset of Chronic Illnesses

In the U.S. safety study in which all subjects received concomitant Hib and pneumococcal conjugate vaccines, 21 subjects (3%) who received PEDIARIX and 14 subjects (4%) who received INFANRIX, ENGERIX-B, and IPV reported new onset of a chronic illness during the period from 1 to 6 months following the last dose of study vaccines. Among the chronic illnesses reported in the subjects who received PEDIARIX, there were 4 cases of asthma and 1 case each of diabetes mellitus and chronic neutropenia. There were 4 cases of asthma in subjects who received INFANRIX, ENGERIX-B, and IPV.

Seizures

In the German safety study over the entire study period, 6 subjects in the group that received PEDIARIX (n = 4,666) reported seizures. Two of these subjects had a febrile seizure, 1 of whom also developed afebrile seizures. The remaining 4 subjects had afebrile seizures, including 2 with infantile spasms. Two subjects reported seizures within 7 days following vaccination (1 subject had both febrile and afebrile seizures, and 1 subject had afebrile seizures), corresponding to a rate of 0.22 seizures per 1,000 doses (febrile seizures 0.07 per 1,000 doses, afebrile seizures 0.14 per 1,000 doses). No subject who received concomitant INFANRIX, Hib vaccine, and OPV (n = 768) reported seizures. In a separate German study that evaluated the safety of INFANRIX in 22,505 infants who received 66,867 doses of INFANRIX administered as a 3-dose primary series, the rate of seizures within 7 days of vaccination with INFANRIX was 0.13 per 1,000 doses (febrile seizures 0.0 per 1,000 doses, afebrile seizures 0.13 per 1,000 doses).

Over the entire study period in the U.S. safety study in which all subjects received concomitant Hib and pneumococcal conjugate vaccines, 4 subjects in the group that received PEDIARIX (n = 673) reported seizures. Three of these subjects had a febrile seizure and 1 had an afebrile seizure. Over the entire study period, 2 subjects in the group that received INFANRIX, ENGERIX-B, and IPV (n = 335) reported febrile seizures. There were no afebrile seizures in this group. No subject in either study group had seizures within 7 days following vaccination.

Other Neurological Events of Interest

No cases of hypotonic-hyporesponsiveness or encephalopathy were reported in either the German or U.S. safety studies.

Safety of PEDIARIX after a Previous Dose of Hepatitis B Vaccine

Limited data are available on the safety of administering PEDIARIX after a previous dose of hepatitis B vaccine. In 2 separate studies, 160 Moldovan infants and 96 U.S. infants, respectively, received 3 doses of PEDIARIX following 1 previous dose of hepatitis B vaccine. Neither study was designed to detect significant differences in rates of adverse events associated with PEDIARIX administered after a previous dose of hepatitis B vaccine compared with PEDIARIX administered without a previous dose of hepatitis B vaccine.

6.2 Postmarketing Safety Surveillance Study

In a safety surveillance study conducted at a health maintenance organization in the United States, infants who received 1 or more doses of PEDIARIX from approximately mid-2003 through mid-2005 were compared with age-, gender-, and area-matched historical controls who received 1 or more doses of separately administered U.S.-licensed DTaP vaccine from 2002 through approximately mid-2003. Only infants who received 7-valent pneumococcal conjugate vaccine (Wyeth Pharmaceuticals Inc.) concomitantly with PEDIARIX or DTaP vaccine were included in the cohorts. Other U.S.-licensed vaccines were administered according to routine practices at the study sites, but concomitant administration with PEDIARIX or DTaP was not a criterion for inclusion in the cohorts. A birth dose of hepatitis B vaccine had been administered routinely to infants in the historical DTaP control cohort, but not to infants who received PEDIARIX. For each of Doses 1-3, a random sample of 40,000 infants who received PEDIARIX was compared with the historical DTaP control cohort for the incidence of seizures (with or without fever) during the 8-day period following vaccination. For each dose, random samples of 7,500 infants in each cohort were also compared for the incidence of medically-attended fever (fever ≥100.4°F that resulted in hospitalization, an emergency department visit, or an outpatient visit) during the 4-day period following vaccination. Possible seizures and medical visits plausibly related to fever were identified by searching automated inpatient and outpatient data files. Medical record reviews of identified events were conducted to verify the occurrence of seizures or medically-attended fever. The incidence of verified seizures and medically-attended fever from this study are presented in Table 2.

Table 2. Percentage of Infants with Seizures (with or without Fever) within 8 Days of Vaccination and Medically-Attended Fever within 4 Days of Vaccination with PEDIARIX Compared with Historical Controls
Adverse Reaction | PEDIARIX |  |  | Historical DTaP Controls |  |  | Difference (PEDIARIX–DTaP Controls)
Adverse Reaction | N | n | %; (95% CI) | N | n | %; (95% CI) | %; (95% CI)
All Seizures; (with or without fever)
Dose 1, Days 0-7 | 40,000 | 7 | 0.02; (0.01, 0.04) | 39,232 | 6 | 0.02; (0.01, 0.03) | 0.00; (-0.02, 0.02)
Dose 2, Days 0-7 | 40,000 | 3 | 0.01; (0.00, 0.02) | 37,405 | 4 | 0.01; (0.00, 0.03) | 0.00; (-0.02, 0.01)
Dose 3, Days 0-7 | 40,000 | 6 | 0.02; (0.01, 0.03) | 40,000 | 5 | 0.01; (0.00, 0.03) | 0.00; (-0.01, 0.02)
Total doses | 120,000 | 16 | 0.01; (0.01, 0.02) | 116,637 | 15 | 0.01; (0.01, 0.02) | 0.00; (-0.01, 0.01)
Medically-Attended Fevera
Dose 1, Days 0-3 | 7,500 | 14 | 0.19; (0.11, 0.30) | 7,500 | 14 | 0.19; (0.11, 0.30) | 0.00; (-0.14, 0.14)
Dose 2, Days 0-3 | 7,500 | 25 | 0.33; (0.22, 0.48) | 7,500 | 15 | 0.20; (0.11, 0.33) | 0.13; (-0.03, 0.30)
Dose 3, Days 0-3 | 7,500 | 21 | 0.28; (0.17, 0.43) | 7,500 | 19 | 0.25; (0.15, 0.39) | 0.03; (-0.14, 0.19)
Total doses | 22,500 | 60 | 0.27; (0.20, 0.34) | 22,500 | 48 | 0.21; (0.16, 0.28) | 0.05; (-0.01, 0.14)
DTaP – any U.S.-licensed DTaP vaccine. Infants received 7-valent pneumococcal conjugate vaccine (Wyeth Pharmaceuticals Inc.) concomitantly with each dose of PEDIARIX or DTaP. Other U.S.-licensed vaccines were administered according to routine practices at the study sites.
N = Number of subjects in the given cohort.
n = Number of subjects with reactions reported in the given cohort.
a Medically-attended fever defined as fever ≥100.4°F that resulted in hospitalization, an emergency department visit, or an outpatient visit.

6.3 Postmarketing Spontaneous Reports for PEDIARIX

In addition to reports in clinical trials for PEDIARIX, the following adverse reactions have been identified during postapproval use of PEDIARIX. Because these reactions are reported voluntarily from a population of uncertain size, it is not always possible to reliably estimate their frequency or establish a causal relationship to vaccine exposure.

Cardiac Disorders

Cyanosis.

Gastrointestinal Disorders

Diarrhea, vomiting.

General Disorders and Administration Site Conditions

Fatigue, injection site cellulitis, injection site induration, injection site itching, injection site nodule/lump, injection site reaction, injection site vesicles, injection site warmth, limb pain, limb swelling.

Immune System Disorders

Anaphylactic reaction, anaphylactoid reaction, hypersensitivity.

Infections and Infestations

Upper respiratory tract infection.

Investigations

Abnormal liver function tests.

Nervous System Disorders

Bulging fontanelle, depressed level of consciousness, encephalitis, hypotonia, hypotonic-hyporesponsive episode, lethargy, somnolence, syncope.

Psychiatric Disorders

Crying, insomnia, nervousness, restlessness, screaming, unusual crying.

Respiratory, Thoracic, and Mediastinal Disorders

Apnea, cough, dyspnea.

Skin and Subcutaneous Tissue Disorders

Angioedema, erythema, rash, urticaria.

Vascular Disorders

Pallor, petechiae.

6.4 Postmarketing Spontaneous Reports for INFANRIX and/or ENGERIX-B

The following adverse reactions have been identified during postapproval use of INFANRIX and/or ENGERIX-B in children younger than 7 years but not already reported for PEDIARIX. Because these reactions are reported voluntarily from a population of uncertain size, it is not always possible to reliably estimate their frequency or establish a causal relationship to vaccine exposure.

Blood and Lymphatic System Disorders

Idiopathic thrombocytopenic purpura,a,b lymphadenopathy,a thrombocytopenia.a,b

Gastrointestinal Disorders

Abdominal pain,b intussusception,a,b nausea.b

General Disorders and Administration Site Conditions

Asthenia,b malaise.b

Hepatobiliary Disorders

Jaundice.b

Immune System Disorders

Anaphylactic shock,a serum sickness–like disease.b

Musculoskeletal and Connective Tissue Disorders

Arthralgia,b arthritis,b muscular weakness,b myalgia.b

Nervous System Disorders

Encephalopathy,a headache,a meningitis,b neuritis,b neuropathy,b paralysis.b

Skin and Subcutaneous Tissue Disorders

Alopecia,b erythema multiforme,b lichen planus,b pruritus,a,b Stevens Johnson syndrome.a

Vascular Disorders

Vasculitis.b

a Following INFANRIX (licensed in the United States in 1997).

b Following ENGERIX-B (licensed in the United States in 1989).

7 DRUG INTERACTIONS

7.1 Concomitant Vaccine Administration

Immune responses following concomitant administration of PEDIARIX, Hib conjugate vaccine (Wyeth Pharmaceuticals Inc.; no longer licensed in the U.S.), and 7-valent pneumococcal conjugate vaccine (Wyeth Pharmaceuticals Inc.) were evaluated in a clinical trial [see Clinical Studies (14.3)].

When PEDIARIX is administered concomitantly with other injectable vaccines, they should be given with separate syringes and at different injection sites. PEDIARIX should not be mixed with any other vaccine in the same syringe.

7.2 Immunosuppressive Therapies

Immunosuppressive therapies, including irradiation, antimetabolites, alkylating agents, cytotoxic drugs, and corticosteroids (used in greater than physiologic doses), may reduce the immune response to PEDIARIX.

8 USE IN SPECIFIC POPULATIONS

8.4 Pediatric Use

Safety and effectiveness of PEDIARIX were established in the age group 6 weeks through 6 months on the basis of clinical studies [see Adverse Reactions (6.1), Clinical Studies (14.1, 14.2)]. Safety and effectiveness of PEDIARIX in the age group 7 months through 6 years are supported by evidence in infants aged 6 weeks through 6 months. Safety and effectiveness of PEDIARIX in infants younger than 6 weeks and children aged 7 to 16 years have not been evaluated.

11 DESCRIPTION

PEDIARIX [Diphtheria and Tetanus Toxoids and Acellular Pertussis Adsorbed, Hepatitis B (Recombinant) and Inactivated Poliovirus Vaccine] is a noninfectious, sterile vaccine for intramuscular administration. Each 0.5-mL dose is formulated to contain 25 Lf of diphtheria toxoid, 10 Lf of tetanus toxoid, 25 mcg of inactivated pertussis toxin (PT), 25 mcg of filamentous hemagglutinin (FHA), 8 mcg of pertactin (69 kiloDalton outer membrane protein), 10 mcg of HBsAg, 40 D-antigen Units (DU) of Type 1 poliovirus (Mahoney), 8 DU of Type 2 poliovirus (MEF-1), and 32 DU of Type 3 poliovirus (Saukett). The diphtheria, tetanus, and pertussis components are the same as those in INFANRIX and KINRIX. The hepatitis B surface antigen is the same as that in ENGERIX-B.

The diphtheria toxin is produced by growing Corynebacterium diphtheriae (C. diphtheriae) in Fenton medium containing a bovine extract. Tetanus toxin is produced by growing Clostridium tetani (C. tetani) in a modified Latham medium derived from bovine casein. The bovine materials used in these extracts are sourced from countries which the United States Department of Agriculture (USDA) has determined neither have nor present an undue risk for bovine spongiform encephalopathy (BSE). Both toxins are detoxified with formaldehyde, concentrated by ultrafiltration, and purified by precipitation, dialysis, and sterile filtration.

The acellular pertussis antigens (PT, FHA, and pertactin) are isolated from Bordetella pertussis (B. pertussis) culture grown in modified Stainer-Scholte liquid medium. PT and FHA are isolated from the fermentation broth; pertactin is extracted from the cells by heat treatment and flocculation. The antigens are purified in successive chromatographic and precipitation steps. PT is detoxified using glutaraldehyde and formaldehyde. FHA and pertactin are treated with formaldehyde.

The hepatitis B surface antigen is obtained by culturing genetically engineered Saccharomyces cerevisiae (S. cerevisiae) cells, which carry the surface antigen gene of the hepatitis B virus, in synthetic medium. The surface antigen expressed in the S. cerevisiae cells is purified by several physiochemical steps, which include precipitation, ion exchange chromatography, and ultrafiltration.

The inactivated poliovirus component is an enhanced potency component. Each of the 3 strains of poliovirus is individually grown in VERO cells, a continuous line of monkey kidney cells, cultivated on microcarriers. Calf serum and lactalbumin hydrolysate are used during VERO cell culture and/or virus culture. Calf serum is sourced from countries the USDA has determined neither have nor present an undue risk for BSE. After clarification, each viral suspension is purified by ultrafiltration, diafiltration, and successive chromatographic steps, and inactivated with formaldehyde. The 3 purified viral strains are then pooled to form a trivalent concentrate.

Diphtheria and tetanus toxoids and pertussis antigens (inactivated PT, FHA, and pertactin) are individually adsorbed onto aluminum hydroxide. The hepatitis B component is adsorbed onto aluminum phosphate.

Diphtheria and tetanus toxoid potency is determined by measuring the amount of neutralizing antitoxin in previously immunized guinea pigs. The potency of the acellular pertussis component (inactivated PT, FHA, and pertactin) is determined by enzyme-linked immunosorbent assay (ELISA) on sera from previously immunized mice. Potency of the hepatitis B component is established by HBsAg ELISA. The potency of the inactivated poliovirus component is determined by using the D-antigen ELISA and by a poliovirus-neutralizing cell culture assay on sera from previously immunized rats.

Each 0.5-mL dose contains aluminum hydroxide and aluminum phosphate as adjuvants (formulated to contain 0.7 mg aluminum) and ≤4.4 mg of sodium chloride. The aluminum content is measured by assay. Each dose also contains ≤100 mcg of residual formaldehyde and ≤100 mcg of polysorbate 80 (Tween 80). Neomycin sulfate and polymyxin B sulfate are used in the poliovirus vaccine manufacturing process and may be present in the final vaccine at ≤0.05 ng neomycin and ≤0.01 ng polymyxin B per dose. The procedures used to manufacture the HBsAg antigen result in a product that contains ≤5% yeast protein.

The tip cap and rubber plunger stopper of the prefilled syringe are not made with natural rubber latex.

PEDIARIX is formulated without preservatives.

12 CLINICAL PHARMACOLOGY

12.1 Mechanism of Action

Diphtheria

Diphtheria is an acute toxin-mediated infectious disease caused by toxigenic strains of C. diphtheriae. Protection against disease is due to the development of neutralizing antibodies to the diphtheria toxin. A serum diphtheria antitoxin level of 0.01 IU/mL is the lowest level giving some degree of protection; a level of 0.1 IU/mL is regarded as protective.^2

Tetanus

Tetanus is an acute toxin-mediated disease caused by a potent exotoxin released by C. tetani. Protection against disease is due to the development of neutralizing antibodies to the tetanus toxin. A serum tetanus antitoxin level of at least 0.01 IU/mL, measured by neutralization assays, is considered the minimum protective level.^3,4 A level ≥0.1 IU/mL is considered protective.^5

Pertussis

Pertussis (whooping cough) is a disease of the respiratory tract caused by B. pertussis. The role of the different components produced by B. pertussis in either the pathogenesis of, or the immunity to, pertussis is not well understood. There is no established serological correlate of protection for pertussis.

Hepatitis B

Infection with hepatitis B virus can have serious consequences including acute massive hepatic necrosis and chronic active hepatitis. Chronically infected persons are at increased risk for cirrhosis and hepatocellular carcinoma.

Antibody concentrations ≥10 mIU/mL against HBsAg are recognized as conferring protection against hepatitis B virus infection.^6

Poliomyelitis

Poliovirus is an enterovirus that belongs to the picornavirus family. Three serotypes of poliovirus have been identified (Types 1, 2, and 3). Poliovirus-neutralizing antibodies confer protection against poliomyelitis disease.^7

13 NONCLINICAL TOXICOLOGY

13.1 Carcinogenesis, Mutagenesis, Impairment of Fertility

PEDIARIX has not been evaluated for carcinogenic or mutagenic potential or for impairment of fertility.

14 CLINICAL STUDIES

The efficacy of PEDIARIX is based on the immunogenicity of the individual antigens compared with licensed vaccines. Serological correlates of protection exist for the diphtheria, tetanus, hepatitis B, and poliovirus components. The efficacy of the pertussis component, which does not have a well-established correlate of protection, was determined in clinical trials of INFANRIX.

14.1 Efficacy of INFANRIX

Efficacy of a 3-dose primary series of INFANRIX has been assessed in 2 clinical studies.

A double-blind, randomized, active Diphtheria and Tetanus Toxoids (DT)-controlled trial conducted in Italy, sponsored by the National Institutes of Health (NIH), assessed the absolute protective efficacy of INFANRIX when administered at 2, 4, and 6 months of age. The population used in the primary analysis of the efficacy of INFANRIX included 4,481 infants vaccinated with INFANRIX and 1,470 DT vaccinees. After 3 doses, the absolute protective efficacy of INFANRIX against WHO-defined typical pertussis (21 days or more of paroxysmal cough with infection confirmed by culture and/or serologic testing) was 84% (95% CI: 76%, 89%). When the definition of pertussis was expanded to include clinically milder disease, with infection confirmed by culture and/or serologic testing, the efficacy of INFANRIX was 71% (95% CI: 60%, 78%) against >7 days of any cough and 73% (95% CI: 63%, 80%) against ≥14 days of any cough. A longer unblinded follow-up period showed that after 3 doses and with no booster dose in the second year of life, the efficacy of INFANRIX against WHO-defined pertussis was 86% (95% CI: 79%, 91%) among children followed to 6 years of age. For details see INFANRIX prescribing information.

A prospective efficacy trial was also conducted in Germany employing a household contact study design. In this study, the protective efficacy of INFANRIX administered to infants at 3, 4, and 5 months of age against WHO-defined pertussis was 89% (95% CI: 77%, 95%). When the definition of pertussis was expanded to include clinically milder disease, with infection confirmed by culture and/or serologic testing, the efficacy of INFANRIX against ≥7 days of any cough was 67% (95% CI: 52%, 78%) and against ≥7 days of paroxysmal cough was 81% (95% CI: 68%, 89%). For details see INFANRIX prescribing information.

14.2 Immunological Evaluation of PEDIARIX

In a U.S. multicenter study, infants were randomized to 1 of 3 groups: (1) a combination vaccine group that received PEDIARIX concomitantly with Hib conjugate vaccine (Wyeth Pharmaceuticals Inc.; no longer licensed in the United States) and U.S.-licensed 7-valent pneumococcal conjugate vaccine (Wyeth Pharmaceuticals Inc.); (2) a separate vaccine group that received U.S.-licensed INFANRIX, ENGERIX-B, and IPV (Sanofi Pasteur SA) concomitantly with the same Hib and pneumococcal conjugate vaccines; and (3) a staggered vaccine group that received PEDIARIX concomitantly with the same Hib conjugate vaccine but with the same pneumococcal conjugate vaccine administered 2 weeks later. The schedule of administration was 2, 4, and 6 months of age. Infants either did not receive a dose of hepatitis B vaccine prior to enrollment or were permitted to receive 1 dose of hepatitis B vaccine administered at least 30 days prior to enrollment. For the separate vaccine group, ENGERIX-B was not administered at 4 months of age to subjects who received a dose of hepatitis B vaccine prior to enrollment. Among subjects in all 3 vaccine groups combined, 84% were White, 7% were Hispanic, 6% were Black, 0.7% were Asian, and 2.4% were of other racial/ethnic groups.

The immune responses to the pertussis (PT, FHA, and pertactin), diphtheria, tetanus, poliovirus, and hepatitis B antigens were evaluated in sera obtained 1 month (range: 20 to 60 days) after the third dose of PEDIARIX or INFANRIX. Geometric mean antibody concentrations (GMCs) adjusted for pre-vaccination values for PT, FHA, and pertactin and the seroprotection rates for diphtheria, tetanus, and the polioviruses among subjects who received PEDIARIX in the combination vaccine group were shown to be non-inferior to those achieved following separately administered vaccines (Table 3).

Because of differences in the hepatitis B vaccination schedule among subjects in the study, no clinical limit for non-inferiority was pre-defined for the hepatitis B immune response. However, in a previous U.S. study, non-inferiority of PEDIARIX relative to separately administered INFANRIX, ENGERIX-B, and an oral poliovirus vaccine, with respect to the hepatitis B immune response was demonstrated.

Table 3. Antibody Responses following PEDIARIX as Compared with Separate Concomitant Administration of INFANRIX, ENGERIX-B, and IPV (1 Montha after Administration of Dose 3) in Infants Vaccinated at 2, 4, and 6 Months of Age when Administered Concomitantly with Hib Conjugate Vaccine and Pneumococcal Conjugate Vaccine (PCV7)
Antibody | PEDIARIX, Hib Vaccine, & PCV7 | INFANRIX, ENGERIX-B, IPV, Hib Vaccine, & PCV7
Antibody | (n = 154-168) | (n = 141-155)
Anti-diphtheria Toxoid
% ≥0.1 IU/mLb | 99.4 | 98.7
Anti-tetanus Toxoid
% ≥0.1 IU/mLb | 100 | 98.1
Anti-PT
% VRc | 98.7 | 95.1
GMCb | 48.1 | 28.6
Anti-FHA
% VRc | 98.7 | 96.5
GMCb | 111.9 | 97.6
Anti-pertactin
% VRc | 91.7 | 95.1
GMCb | 95.3 | 80.6
Anti-polio 1
% ≥1:8b,d | 100 | 100
Anti-polio 2
% ≥1:8b,d | 100 | 100
Anti-polio 3
% ≥1:8b,d | 100 | 100
 | (n = 114-128) | (n = 111-121)
Anti-HBsAge
% ≥10 mIU/mLf | 97.7 | 99.2
GMC (mIU/mL)f | 1032.1 | 614.5
Hib conjugate vaccine (Wyeth Pharmaceuticals Inc.; no longer licensed in the United States); PCV7 (Wyeth Pharmaceuticals Inc.); IPV (Sanofi Pasteur SA).
Assay methods used: ELISA for anti-diphtheria, anti-tetanus, anti-PT, anti-FHA, anti-pertactin, and anti-HBsAg; micro-neutralization for anti-polio (1, 2, and 3).
VR = Vaccine response: In initially seronegative infants, appearance of antibodies (concentration ≥5 EL.U./mL); in initially seropositive infants, at least maintenance of pre-vaccination concentration.
GMC = Geometric mean antibody concentration. GMCs are adjusted for pre-vaccination levels.
a One-month blood sampling, range: 20 to 60 days.
b Seroprotection rate or GMC for PEDIARIX not inferior to separately administered vaccines (upper limit of 90% CI on GMC ratio [separate vaccine group/combination vaccine group] <1.5 for anti-PT, anti-FHA, and anti-pertactin, and upper limit of 95% CI for the difference in seroprotection rates [separate vaccine group minus combination vaccine group] <10% for diphtheria and tetanus and <5% for the 3 polioviruses). GMCs are adjusted for pre-vaccination levels.
c The upper limit of 95% CI for differences in vaccine response rates (separate vaccine group minus combination group) was 0.31, 1.52, and 9.46 for PT, FHA, and pertactin, respectively. No clinical limit defined for non-inferiority.
d Poliovirus-neutralizing antibody titer.
e Subjects who received a previous dose of hepatitis B vaccine were excluded from the analysis of hepatitis B seroprotection rates and GMCs presented in the table.
f No clinical limit defined for non-inferiority.

14.3 Concomitant Vaccine Administration

In a U.S. multicenter study [see Clinical Studies (14.2)], there was no evidence for interference with the immune responses to PEDIARIX when administered concomitantly with 7-valent pneumococcal conjugate vaccine (Wyeth Pharmaceuticals Inc.) relative to 2 weeks prior.

Anti-PRP (Hib polyribosyl-ribitol-phosphate) seroprotection rates and GMCs of pneumococcal antibodies 1 month (range: 20 to 60 days) after the third dose of vaccines for the combination vaccine group and the separate vaccine group from the U.S. multicenter study [see Clinical Studies (14.2)], are presented in Table 4.

Table 4. Anti-PRP Seroprotection Rates and GMCs (mcg/mL) of Pneumococcal Antibodies 1 Montha following the Third Dose of Hib Conjugate Vaccine and Pneumococcal Conjugate Vaccine (PCV7) Administered Concomitantly with PEDIARIX or with INFANRIX, ENGERIX-B, and IPV
 | PEDIARIX, Hib Vaccine, & PCV7 | INFANRIX, ENGERIX-B, IPV, Hib Vaccine, & PCV7
 | (n = 161-168) | (n = 146-156)
 | % (95% CI) | % (95% CI)
Anti-PRP
≥0.15 mcg/mL | 100 (97.8, 100) | 99.4 (96.5, 100)
Anti-PRP
≥1.0 mcg/mL | 95.8 (91.6, 98.3) | 91.0 (85.3, 95.0)
 | GMC (95% CI) | GMC (95% CI)
Pneumococcal Serotype
4 | 1.7 (1.5, 2.0) | 2.1 (1.8, 2.4)
6B | 0.8 (0.7, 1.0) | 0.7 (0.5, 0.9)
9V | 1.6 (1.4, 1.8) | 1.6 (1.4, 1.9)
14 | 4.7 (4.0, 5.4) | 6.3 (5.4, 7.4)
18C | 2.6 (2.3, 3.0) | 3.0 (2.5, 3.5)
19F | 1.1 (1.0, 1.3) | 1.1 (0.9, 1.2)
23F | 1.5 (1.2, 1.8) | 1.8 (1.5, 2.3)
Hib conjugate vaccine (Wyeth Pharmaceuticals Inc.; no longer licensed in the United States); PCV7 (Wyeth Pharmaceuticals Inc.); IPV (Sanofi Pasteur SA).
Assay method used: ELISA for anti-PRP and 7 pneumococcal serotypes.
GMC = Geometric mean antibody concentration.
a One-month blood sampling, range: 20 to 60 days.

15 REFERENCES

1. Centers for Disease and Control and Prevention. Recommended immunization schedules for persons aged 0-18 years—United States, 2010. MMWR. 2010;58(51&52).
2. Vitek CR and Wharton M. Diphtheria Toxoid. In: Plotkin SA, Orenstein WA, and Offit PA, eds. Vaccines. 5th ed. Saunders;2008:139-156.
3. Wassilak SGF, Roper MH, Kretsinger K, and Orenstein WA. Tetanus Toxoid. In: Plotkin SA, Orenstein WA, and Offit PA, eds. Vaccines. 5th ed. Saunders;2008:805-839.
4. Department of Health and Human Services, Food and Drug Administration. Biological products; Bacterial vaccines and toxoids; Implementation of efficacy review; Proposed rule. Federal Register. December 13, 1985;50(240):51002-51117.
5. Centers for Disease Control and Prevention. General Recommendations on Immunization. Recommendations of the Advisory Committee on Immunization Practices (ACIP). MMWR. 2006;55(RR-15):1-48.
6. Ambrosch F, Frisch-Niggemeyer W, Kremsner P, et al. Persistence of vaccine-induced antibodies to hepatitis B surface antigen and the need for booster vaccination in adult subjects. Postgrad Med J. 1987;63(Suppl. 2):129-135.
7. Sutter RW, Pallansch MA, Sawyer LA, et al. Defining surrogate serologic tests with respect to predicting protective vaccine efficacy: Poliovirus vaccination. In: Williams JC, Goldenthal KL, Burns DL, Lewis Jr BP, eds. Combined vaccines and simultaneous administration. Current issues and perspectives. New York, NY: The New York Academy of Sciences; 1995:289-299.

16 HOW SUPPLIED/STORAGE AND HANDLING

Product: 50090-7541

NDC: 50090-7541-1 .5 mL in a SYRINGE / 10 in a CARTON

17 PATIENT COUNSELING INFORMATION

Provide the following information to the parent or guardian:

- Inform of the potential benefits and risks of immunization with PEDIARIX, and of the importance of completing the immunization series.
- Inform about the potential for adverse reactions that have been temporally associated with administration of PEDIARIX or other vaccines containing similar components.
- Instruct to report any adverse events to their healthcare provider.
- Give the Vaccine Information Statements, which are required by the National Childhood Vaccine Injury Act of 1986 to be given prior to immunization. These materials are available free of charge at the Centers for Disease Control and Prevention (CDC) website (www.cdc.gov/vaccines).

Trademarks are owned by or licensed to the GSK group of companies.

Manufactured by GlaxoSmithKline Biologicals

Rixensart, Belgium, U.S. License 1617, and

GSK Vaccines GmbH

Marburg, Germany, U.S. License 1617

Distributed by GlaxoSmithKline

Durham, NC 27701

©2024 GSK group of companies or its licensor.

PDX:29PI